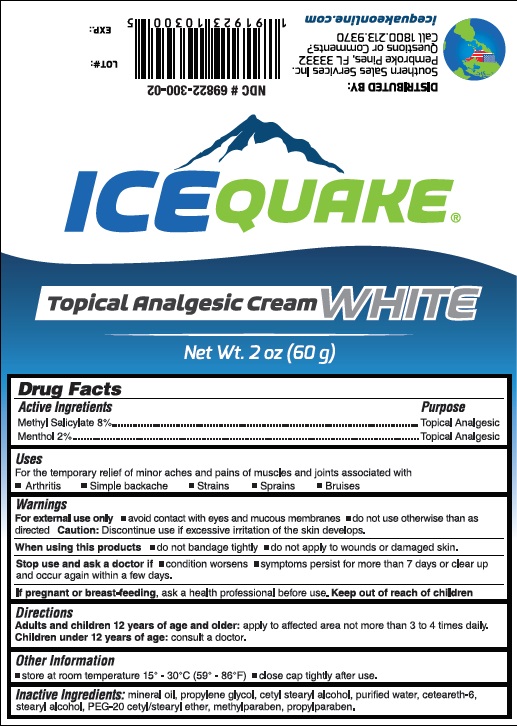 DRUG LABEL: ICE QUAKE Analgesic Cream White
NDC: 69822-300 | Form: CREAM
Manufacturer: Southern Sales & Service, Inc.
Category: otc | Type: HUMAN OTC DRUG LABEL
Date: 20091030

ACTIVE INGREDIENTS: METHYL SALICYLATE 8.0 1/1 1; MENTHOL 2.0 1/1 1
INACTIVE INGREDIENTS: MINERAL OIL; PROPYLENE GLYCOL; CETOSTEARYL ALCOHOL; WATER; CETEARETH-6; STEARYL ALCOHOL; POLYETHYLENE GLYCOL, UNSPECIFIED; METHYLPARABEN; PROPYLPARABEN

ICE QUAKE Analgesic Cream White(Methyl Salicylate and Menthol)

Active Ingredients

Methyl Salicylate 8%

Menthol 2%

Purpose

Topical Analgesic

Uses

Temporarily relieves minor aches and pains of muscles and joints due to:

- arthritis
- simple backache
- bruises
- strains
- sprains

Warnings

For external use only.

If pregnant or breast-feeding, ask a health professional before use.

When using this product

- use only as directed
- Avoid contact with eyes and mucous membranes
- do not bandage tightly or use with a heating devices
- do not apply to wounds or damaged skin
- Do not apply to irritated skin

Stop use and ask a doctor if

- condition worsens
- redness is present
- irritation develops

Keep out of reach of children.

If swallowed, get medical help or contact a Poison Control Center Immediately.

Directions

Adults and Children 12 Years of Age or Older

- Apply generously to affected area
- Massage into painfil area until thoroughly absorbed into skin
- Repeat as necessary, but no more than 3 to 4 times daily

INACTIVE INGREDIENT

Mineral oil, Propylene glycol, Cetyl stearyl alcohol, Purified water, Ceteareth-6, Stearyl alcohol, PEG-20 Cetyl/Stearyl Ether, Methylparaben, propylparaben.

PACKAGE LABEL

Analgesic Cream White

MENTHOL 2%, METHYL SALICYLATE 8%

NET WT 2 OZ (60 g)

Store: At Room Temperature 15° - 30°C (59°- 86°F). Close cap tightly after use.

Distribute By: SSS group, LLC

Pembroke Pines, FL 33332

Questions or Commnets?

Call 800.213.9370